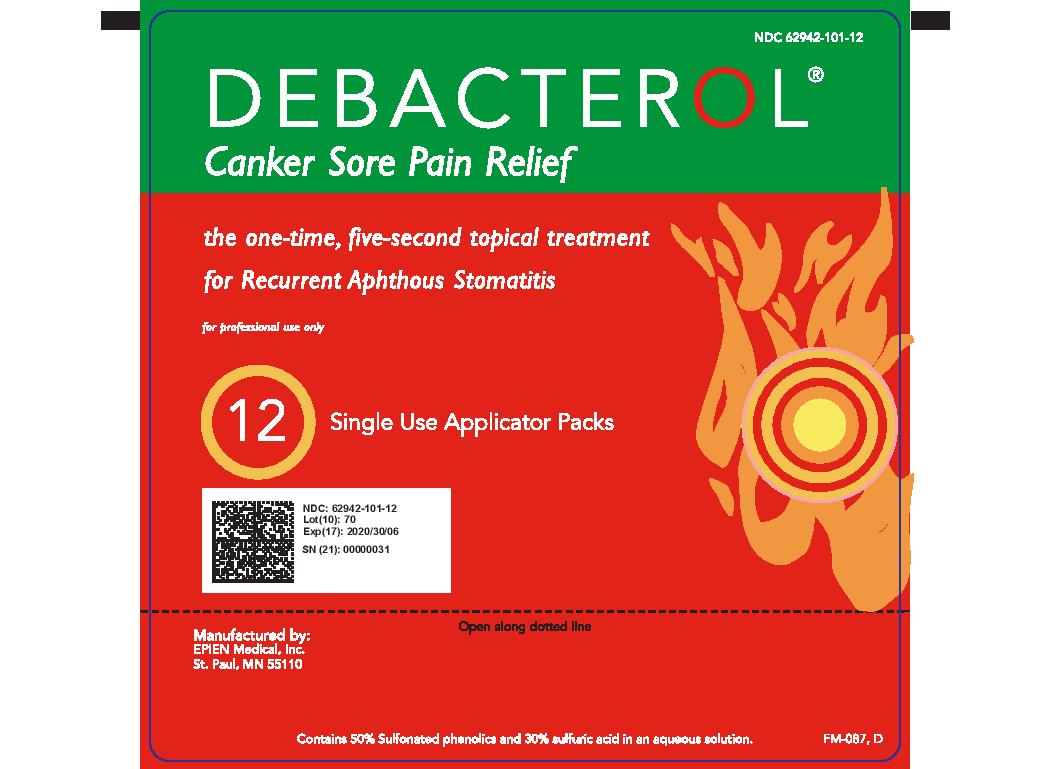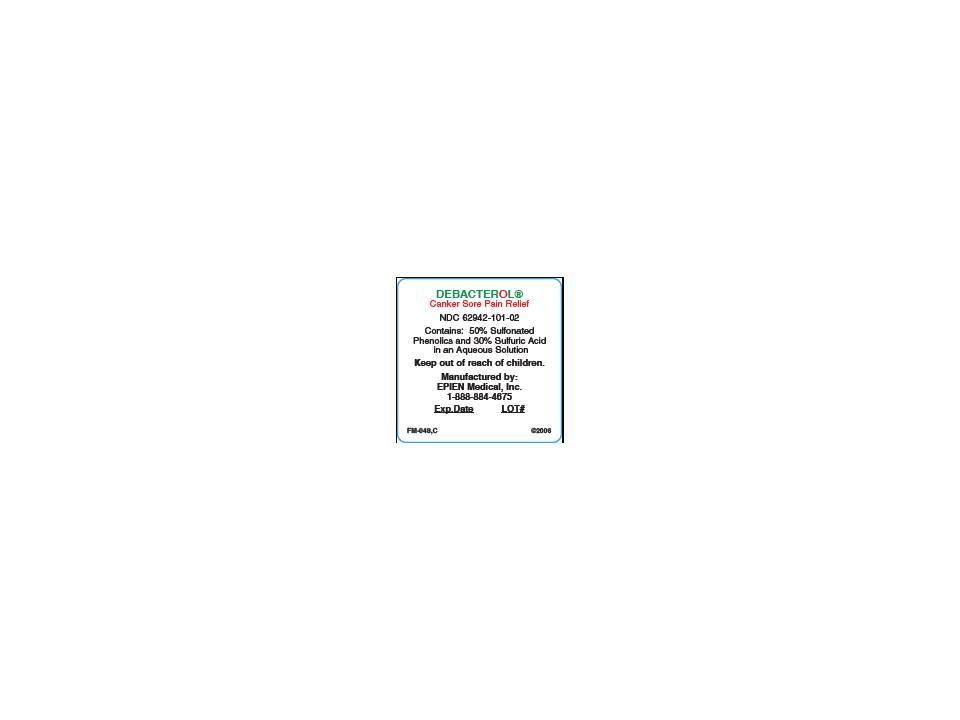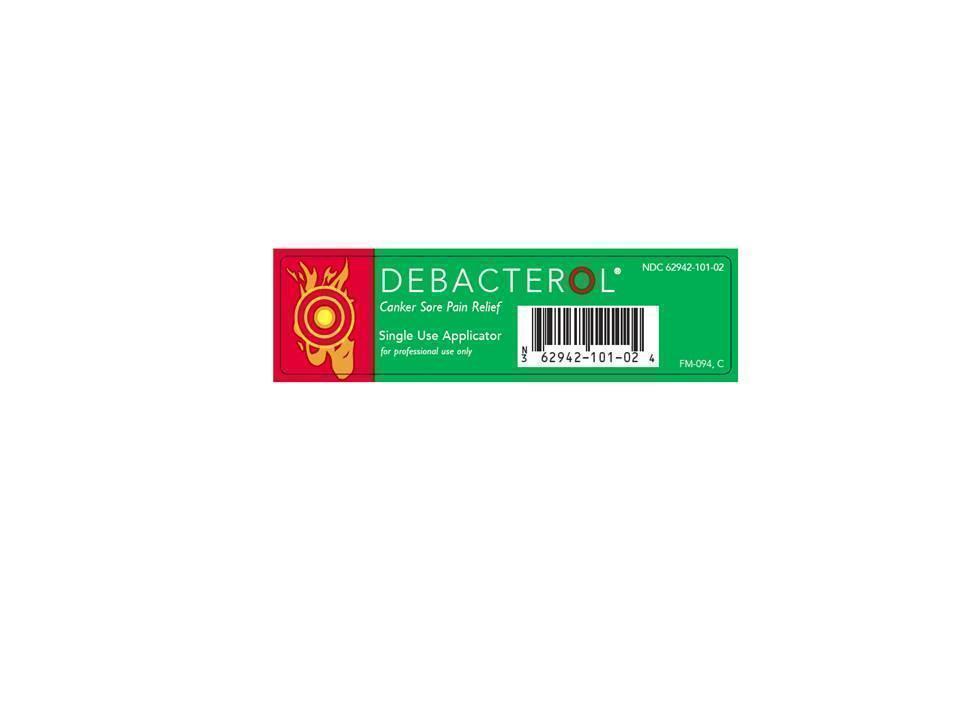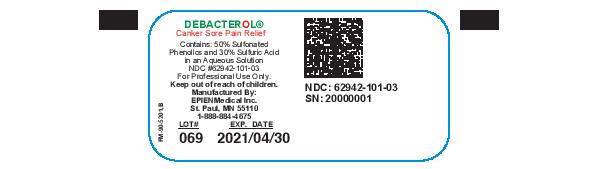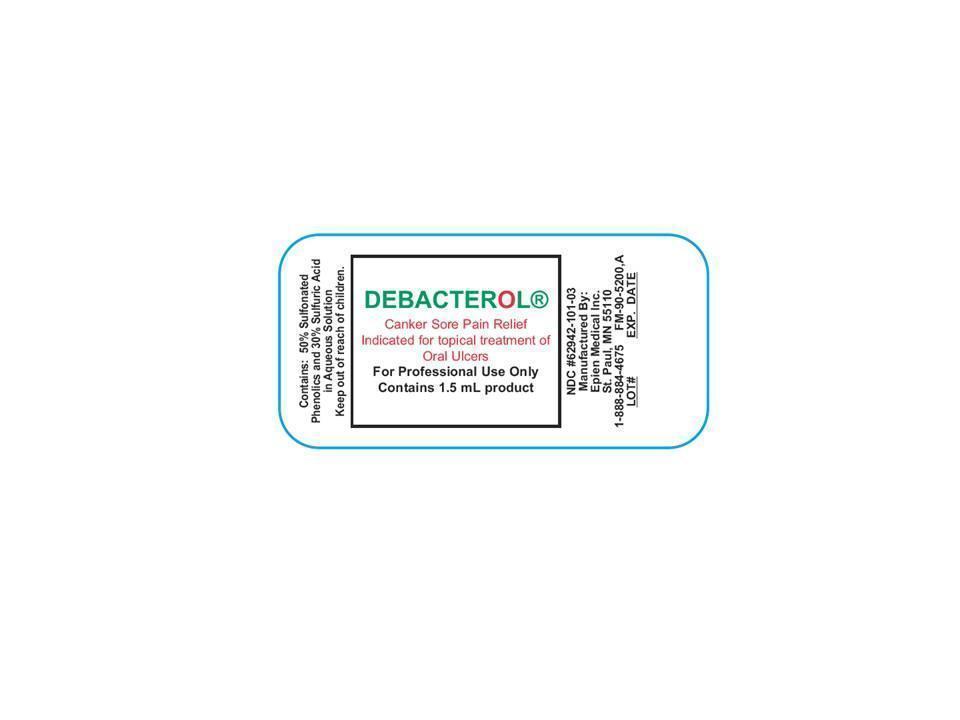 DRUG LABEL: DEBACTEROL Canker Sore Pain Relief
NDC: 62942-101 | Form: SOLUTION
Manufacturer: EPIEN Medical Inc
Category: prescription | Type: HUMAN PRESCRIPTION DRUG LABEL
Date: 20211130

ACTIVE INGREDIENTS: PHENOLSULFONIC ACID 0.5 g/1 mL; SULFURIC ACID 0.3 g/1 mL
INACTIVE INGREDIENTS: WATER 0.2 g/1 mL

DEBACTEROL Canker Sore Pain Relief

DESCRIPTION

Debacterol is a dark brown, semi-viscous liquid. It contains sulfonated phenolics and sulfuric acid, which are tissue denaturants, in an aqueous solution.

DOSAGE FORMS AND STRENGTHS

Contains 50% Sulfonated phenolics and 30% sulfuric acid in an aqueous solution.

INDICATIONS AND USAGE

Debacterol is indicated in the topical treatment of ulcerating lesions of the oral cavity such as Recurrent Aphthous Stomatitis (Canker Sores). Debacterol provides relief from the pain and discomfort of oral mucosal ulcers. Debacterol is not intended for the treatment of vesicular lesions, such as Cold Sores or Fever Blisters.

INSTRUCTIONS FOR USE

Immediately before applying Debacterol thoroughly dry the ulcerated area of oral mucosa that is to be treated using a cotton-tipped applicator, or by usiing some similar method.

For Swab:

After drying the lesion, hold the Debacterol applicator swab with the colored ring end up. Bend the colored ring tip gently to the side until it "snaps" to release the liquid inside. Liquid flows down into the white cotton tip applicator. Apply the Debacterol - coated applicator tip to the dried ulcer area for at least 5 seconds.

For Vial:

After drying the lesion, dip the tip of a cotton tipped applicator into the Debacterol, until it is coated with sufficient agent to coat the entire ulcerated area. Apply the Debacterol - coated applicator tip to the dried ulcer area for at least 5 seconds.

Use a rolling motion to completely cover the entire ulcer bed and ulcer rim. A "stinging" sensation is experienced immediately upon application of the Debacterol to the ulcer. Do not hold the applicator on the ulcer for more than 10 seconds. Debactorol will not harm the normal oral mucosa when used as directed. Thoroughly rinse out the mouth with water and spit out the rinse water. The stinging sensation and ulcer pain will subside almost immediately after the water rinse. One application per ulcer treatment is usually sufficient. However, if the ulcer pain returns shortly after rinsing with water, it is an indication that some part of the ulcer was not covered. Repeat application one more time following the directions above.

It is not recommended that more than one treatment session be performed on an individual mucosal ulcer.

Keep out of reach of children. Do not use if allergic to a material that contains sulfur in any form. Because of its nature, prolonged use of Debacterol on normal tissue should be avoided. Debacterol will eventually necrotize and slough all tissue to which it is applied sufficient volume and should be applied carefully. Debacterol may be harmful with swallowed. If ingested do not induce vomiting. Immediately get medical help or contact a Poison Control Center. If eye exposure occurs, immediately remove any contact lenses and irrigate eyes for at least 15 minutes with lukewarm water and contact a physician.

PRECAUTIONS

Debacterol is for use in the oral cavity only. Avoid eye contact. Saftey and effectiveness in pregnant women and children under the age of 12 has not been established.

ADVERSE REACTIONS

Debacterol may cause local irritation upon administration. If excess irritation occurs during use, a rinse with sodium bicarbonate (baking soda) solution will neutralize the reaction (use 0.5 teaspoon in 120ml of water). If condition persists contact a health care professional.

HOW SUPPLIED

Swab contains 0.2 ml of product. (NDC-62942-101-02)

Vial contains 1.5 ml of product. (NDC-62942-101-03)

STORAGE AND HANDLING

Store at room temperature, 15°C-30°C or 59°F-86°F.

Principal Display Panel - DEBACTEROL SINGLE USE APPLICATOR FRONT LABEL

Debacterol Single Use Applicator - DEBACTEROL SINGLE USE APPLICATOR FRONT LABEL FRONT LABEL

Principal Display Panel - DEBACTEROL SINGLE USE APPLICATOR BACK LABEL

DEBACTEROL SINGLE USE - DEBACTEROL SINGLE USE APPLICATOR BACK LABEL

PRINCIPAL DISPLAY PANEL - DEBACTEROL 12 PACK LABEL

DEBACTEROL 12 PACK LABEL

PRINCIPAL DISPLAY PANEL - DEBACTEROL VIAL LABEL

DEBACTEROL VIAL LABEL